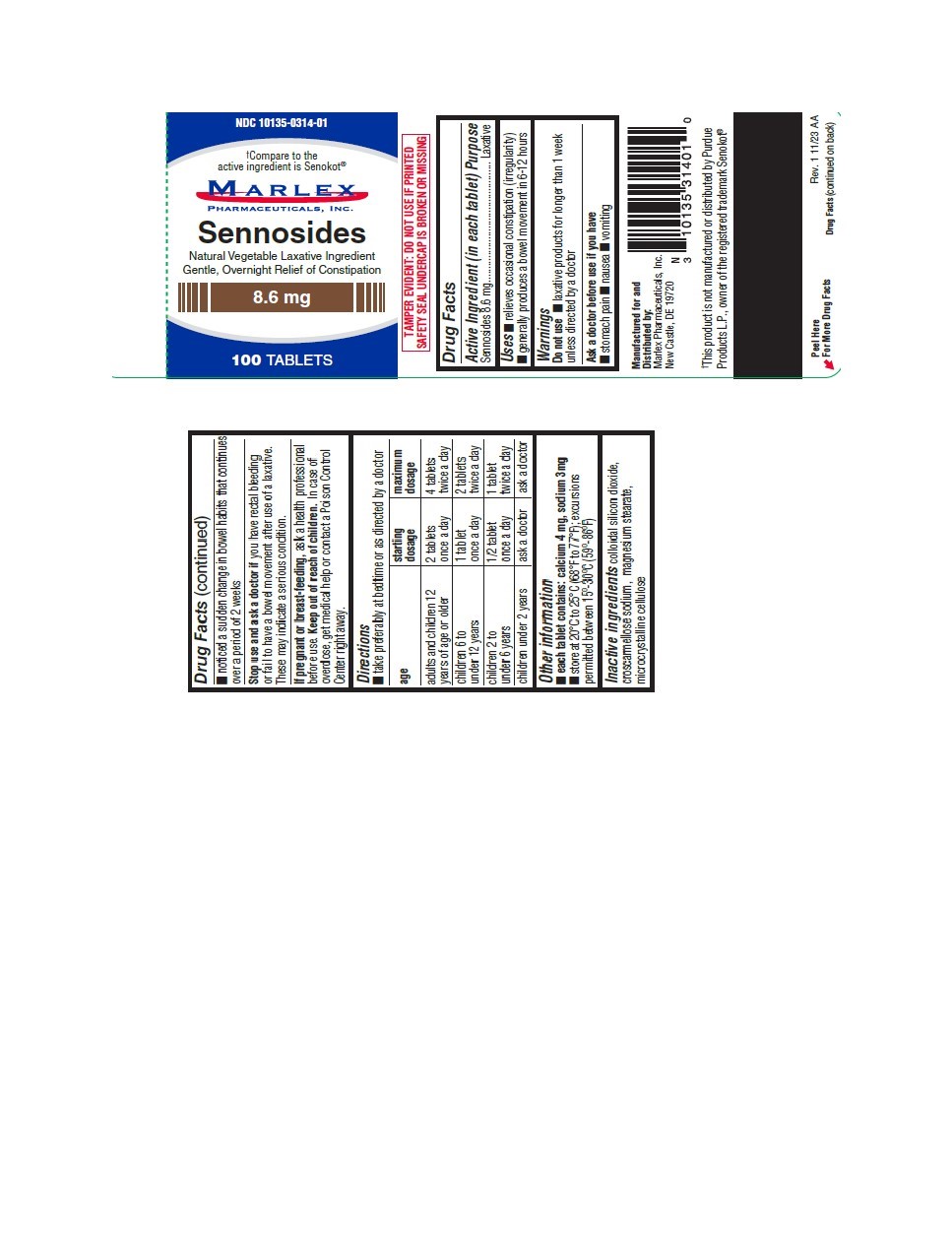 DRUG LABEL: Sennosides
NDC: 10135-314 | Form: TABLET
Manufacturer: Marlex Pharmaceuticals Inc
Category: otc | Type: HUMAN OTC DRUG LABEL
Date: 20251121

ACTIVE INGREDIENTS: SENNOSIDES 8.6 mg/1 1
INACTIVE INGREDIENTS: SILICON DIOXIDE; CROSCARMELLOSE SODIUM; HYPROMELLOSES; MAGNESIUM STEARATE; CELLULOSE, MICROCRYSTALLINE; STEARIC ACID

Sennosides

SENNOSIDES 8.6mg Tablet

Marlex Pharmaceuticals, Inc.

Disclaimer: Most OTC drugs are not reviewed and approved by FDA, however they may be marketed if they comply with applicable regulations and policies. FDA has not evaluated whether this product complies.

----------

Drug Facts

Active ingredient (in each tablet)

Sennosides 8.6 mg

Purpose

Laxative

Uses

- relieves occasional constipation (irregularity)
- generally produces a bowel movement in 6-12 hours

Warnings

Do not use

- laxative products for longer than 1 week unless directed by a doctor

Ask a doctor before use if you have

- stomach Pain
- Nausea
- Vomiting
- noticed a sudden change in bowel habits that continues over a period of 2 weeks

Stop use and ask a doctor if

you have rectal bleeding or fail to have a bowel movement after use of a laxative. These may indicate a serious condition.

If pregnant or breast-feeding,

ask a health professional before use.

Keep out of reach of children.

In case of overdose, get medical help or contact a Poison Control Center right away.

Directions

- take preferably at bedtime or as directed by a doctor

age | starting dosage | maximum dosage
adults and children 12 years of age and older | 2 tablets once a day | 4 tablets twice a day
children 6 to under 12 years of age | 1 tablet once a day | 2 tablets twice a day
children 2 to under 6 years of age | 1/2 tablet once a day | 1 tablet twice a day
children under 2 years | ask a doctor | ask a doctor

Other information

- Each tablet contains: Calcium 4 mg, Sodium 3mg
- Store at 20°C to 25°C (68°F to 77°F) excursions permitted between 15° to 30°C (59°-86°F).

Inactive ingredients

Colloidal silicon dioxide, croscarmellose sodium, magnesium stearate, microcrystalline cellulose.

*Compare to Senokot®

Product color may vary slightly due to nature of ingredients.

*Marlex Pharmaceuticals, Inc. is not affiliated with the owner of the registered trademark Senokot®.

PRINCIPAL DISPLAY PANEL

NDC 10135-0314-01
Sennosides
8.6 mg
100 TABLETS